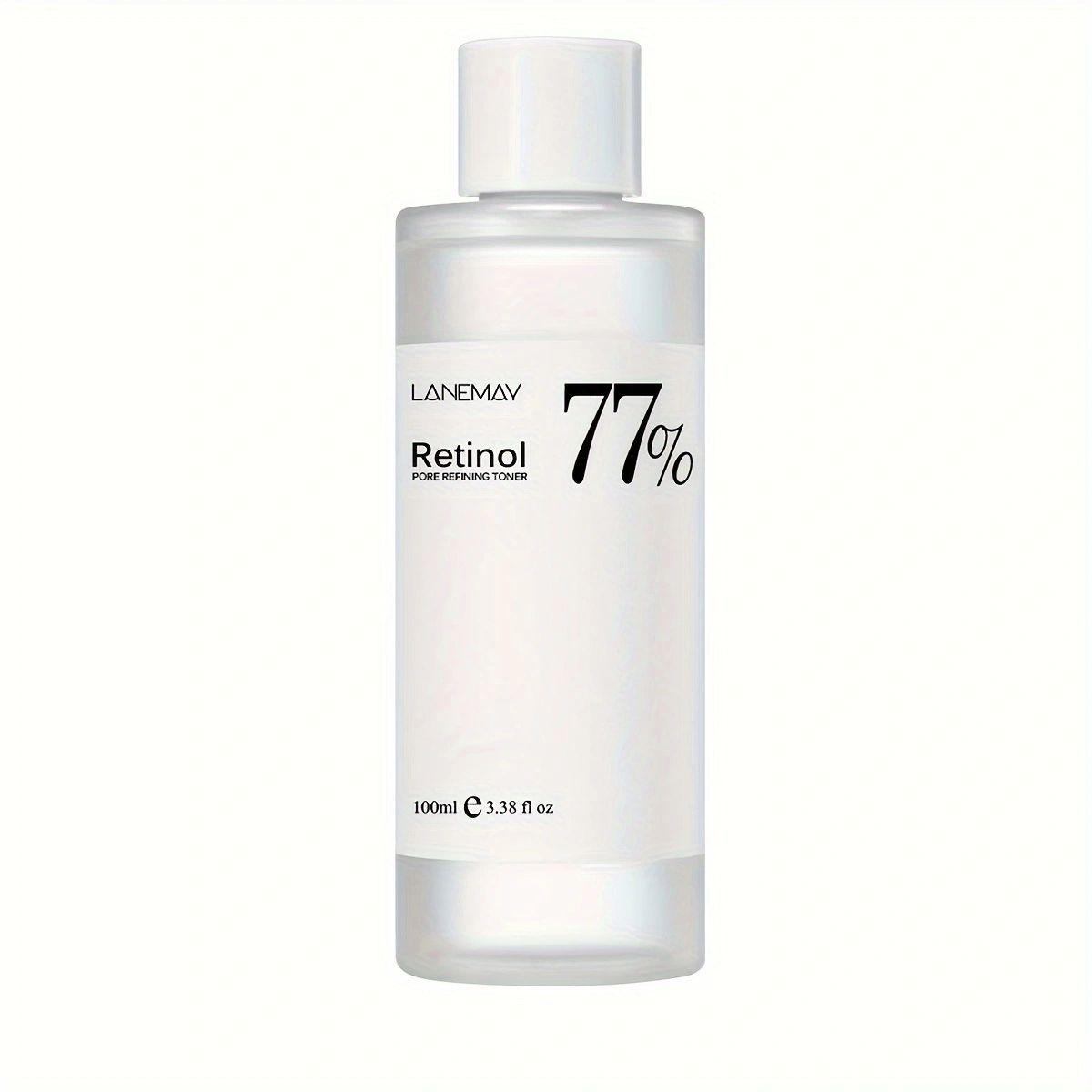 DRUG LABEL: RETINOL PORE REFINING TONER
NDC: 84025-213 | Form: LIQUID
Manufacturer: Guangzhou Yanxi Biotechnology Co., Ltd
Category: otc | Type: HUMAN OTC DRUG LABEL
Date: 20241014

ACTIVE INGREDIENTS: BIOTINOYL TRIPEPTIDE-1 5 mg/100 mL; BUTYLENE GLYCOL 3 mg/100 mL
INACTIVE INGREDIENTS: WATER

DOSAGE AND ADMINISTRATION

Apply to affected area twice per day on cleansed skin.

WARNINGS

keep out of children

INACTIVE INGREDIENT

Aqua

INDICATIONS AND USAGE

For daily skin care

keep out of children

PURPOSE

Deep hydration,moisturizing the skin